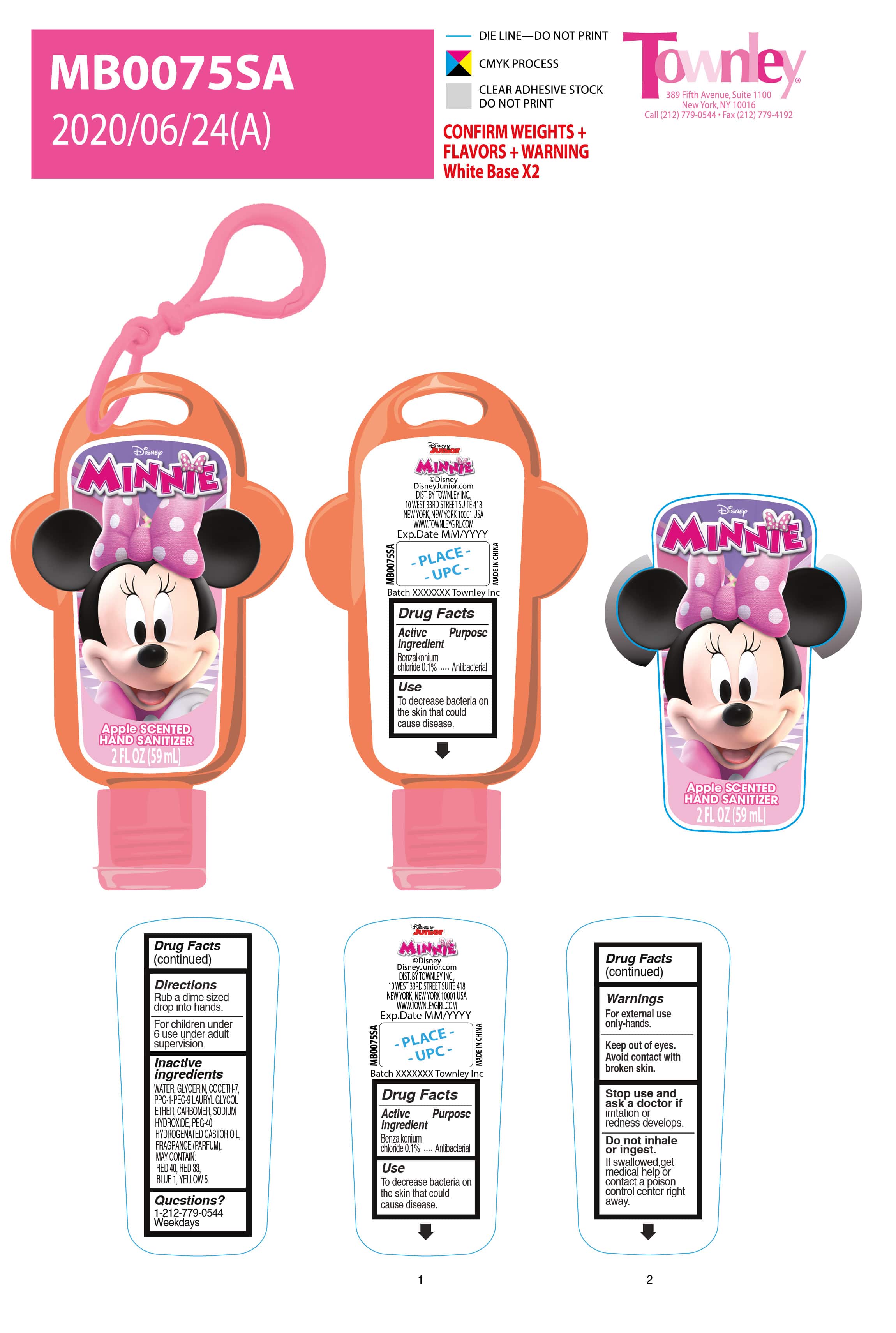 DRUG LABEL: Apple scented hand sanitizer
NDC: 77901-013 | Form: GEL
Manufacturer: Foshan Astar Industry Co., Ltd
Category: otc | Type: HUMAN OTC DRUG LABEL
Date: 20210707

ACTIVE INGREDIENTS: BENZALKONIUM CHLORIDE 0.1 g/100 mL
INACTIVE INGREDIENTS: COCETH-7 0.68 mL/100 mL; PPG-1-PEG-9 LAURYL GLYCOL ETHER 0.68 mL/100 mL; WATER O-18 96 mL/100 mL; GLYCERIN 1.5 mL/100 mL; CARBOMER 934 0.24 mL/100 mL; SODIUM HYDROXIDE 0.12 mL/100 mL; HYDROGENATED CASTOR OIL 0.15 mL/100 mL; FD&C YELLOW NO. 5 0.005 g/100 mL; APPLE 0.3 mL/100 mL; FD&C RED NO. 40 0.003 g/100 mL

MB0075SA，light orange, apple
Foshan Astar

Active ingredient purpose

Benzalkonium chloride 0.1% Antibacterial

Use

To decrease bacteria on the skin that could cause disease.

Warnings

For external use only-hands

keep out of eyes- avoid contact with broken skin

Stop use and ask a dosctor if irritation or radness develops

Do not inhale or ingest. If swallowed, get medical help or contact a poison control right away.

Direction

Rub a dime sized drop into hands.

For children under 6 use under adult supervision

Inactive ingredients

INACTIVE INGREDIENTS: WATER, GLYCERIN, COCETH-7, PPG-1-PEG-9 LAURYL GLYCOL ETHER, CARBOMER, SODIUM HYDROXIDE, PEG-40 HYDROGENATED CASTOR OIL, FRAGRANCE (PARFUM).
MAY CONTAIN: RED 40, RED 33, BLUE 1, YELLOW 5.

Questions?

1-212-779-0544 weekdays